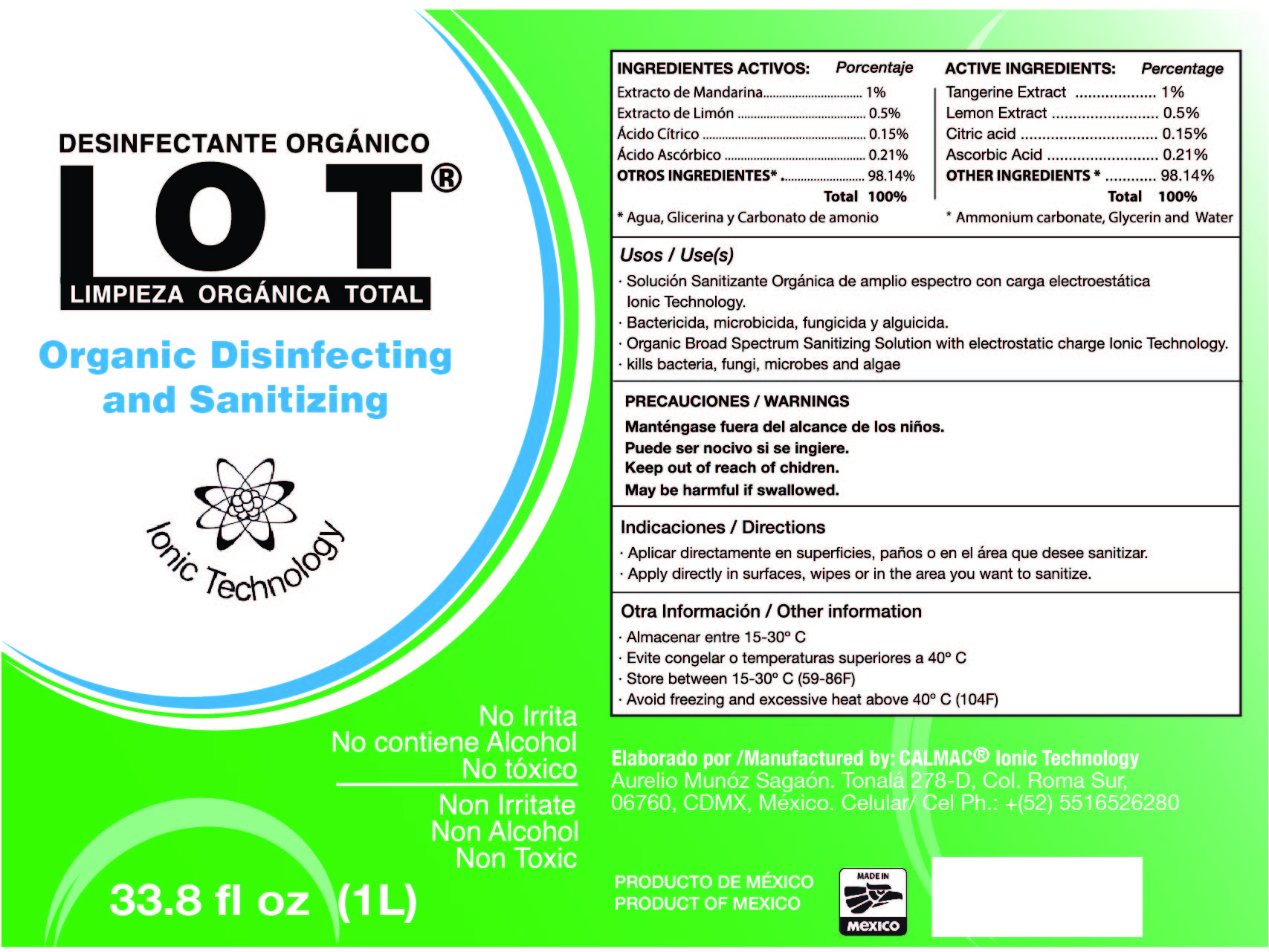 DRUG LABEL: LOT
NDC: 78746-002 | Form: LIQUID
Manufacturer: Aurelio Muñoz Sagaón
Category: otc | Type: HUMAN OTC DRUG LABEL
Date: 20200606

ACTIVE INGREDIENTS: CITRIC ACID MONOHYDRATE 0.15 g/100 g
INACTIVE INGREDIENTS: WATER 98.75 g/100 g; AMMONIUM CARBONATE 0.1 g/100 g; GLYCERIN 1 g/100 g

Inactive Ingredients

ammonium carbonate, glycerin, water.

Active ingredients

Citric acid 0.15% Purpose: Antiseptic

Ascorbic acid 0.21% Purpose: Antiseptic

Warnings

For external use only. Flammable. Keep away from heat or flame.

Use(s)

Hand Sanitizer to help reduce bacteria that potentially can cause disease. For use when soap and water are not available.

Do not use

In children less than 2 months of age

On open skin wounds

When using this product

keep out of eyes, ears and mouth. In case of contact with eyes, rinse eyes thoroughly

with water.

Ask a doctor

If irritation or rash occurs. This may be a sign of a serious condition.

KEEP OUT OF REACH OF CHILDREN

If swallowed, get medical help or contact a Poison Control Center right away.

Other information

Store between 15-30C (59-86F)

Avoid freezing and excessive heat above 40C (104F)

Directions

Place enough product on hands to cover all surfaces. Rub hands together until dry.

Supervise children under 6 years old of age when using this product to avoid swallowing.

Purpose

Purpose: Antiseptic

Package label- Principal Display Panel

1000 mL NDC: 78746-002-01